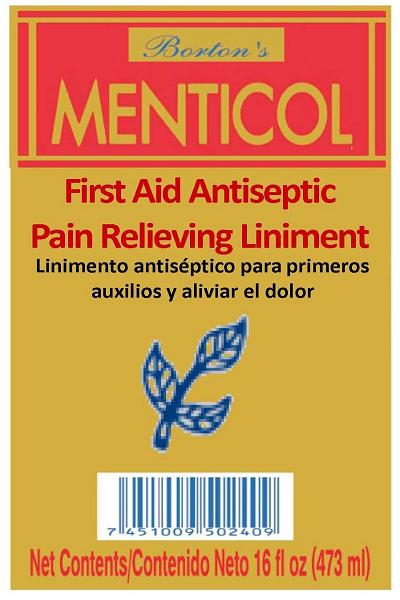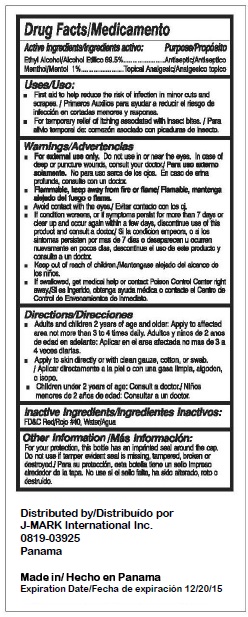 DRUG LABEL: Bortons Menticol
NDC: 50790-200 | Form: LIQUID
Manufacturer: J-Mark International Inc
Category: otc | Type: HUMAN OTC DRUG LABEL
Date: 20100514

ACTIVE INGREDIENTS: ALCOHOL 69.5 mL/100 mL; MENTHOL 1 mL/100 mL
INACTIVE INGREDIENTS: WATER

Borton's Menticol

ACTIVE INGREDIENT

Drug Facts/Medicamento

Active Ingredients/Ingredients activo Purpose/Proposito

Ethyl Alcohol/Alcohol Etilico 69.5% Antiseptic/Antiseptico

Methol/Mentol 1% Topical Anagesic/Anagesico topico

PURPOSE

USES/USO

First Aid to help reduce the risk of infection in minor cuts and scrapes/Primeros Auxillos para ayudar a reducir el riegsgo de infeccion en cortadas menores y raspones

For temporary relief of itching associated with insect bites. Para ailvio temporal de: comezon asociado con picaduras de insecto

Warnings/Advertencias

For external use only. do not use in or near the eyes. In case of deep or puncture wounds consult your doctor/ Para uso externo solamente. No para uso serca de los ojos. En caso de erina profunda, consulte con un doctor

Flammable, keep away from fire or flame. Flamable, mantenga alejado del fuego or flama

Avoid contact with the eyes/Eveitar contacto con los oj

If condition worsens or if symptoms persist for more than 7 days or clear up and occur again within a few days, discontinue use of this product and consult a doctor./Si la condicion empeora o si los sintomas persisten por mas de 7 dias o desaparecen u ocurren nuevamente en pocos dias, descontinue el uso de este producto y consulte a un doctor

Keep out of reach of children/Mantengase alejado del alcance de los ninos

If swallowed, get medical help or contact Poison Control Center right away. Si es ingerido, obtenga ayuda medica o contacte el centro de control de envenamientos de inmediato.

DOSAGE AND ADMINISTRATION

DIRECTIONS/DIRECCIONES

Adults and children 2 years of age and older: apply to affected area not more than 3 to 4 times daily. Adultos y ninos de 2 anos de edad en adelante: Aplica en el area afectada no mas de 3 a 4 veces diarias

Apply to skin directly or with clean gauze, cotton, or swab./Aplicar directamente a la piel o con una gasa limpia, algodon, o isopo

Children under 2 years of age: consult a doctor/Ninos menores de 2 anos de edad: consultar a un doctor.

INACTIVE INGREDIENT

FDandC Red/Rojo 40, water/ agua

PATIENT COUNSELING INFORMATION

For you protection, this bottle has an imprinted seal around the cap. Do not use if tamper evident seal is missing, tampered, broken or destroyed./Para su proteccion, esta botella tiene un sello impreso alrededor de la tapa. No use si el sello falta, ha sido alterado, roto o destruido

Distributed by/Distribuido por

J-MARK International Inc.

0819-03925

Panama

Made In/Hecho en Panama

Expiration Date/Fecha de Expiracion 12/2015

PACKAGE LABEL

Borton's Menticol

First Aid Antiseptic

Pain Relieving Liniment

Linimentoantiseptico para primeros

auxilios y aliviar el dolor

Net contents/Contenido Neto 16 fl oz (473 ml)